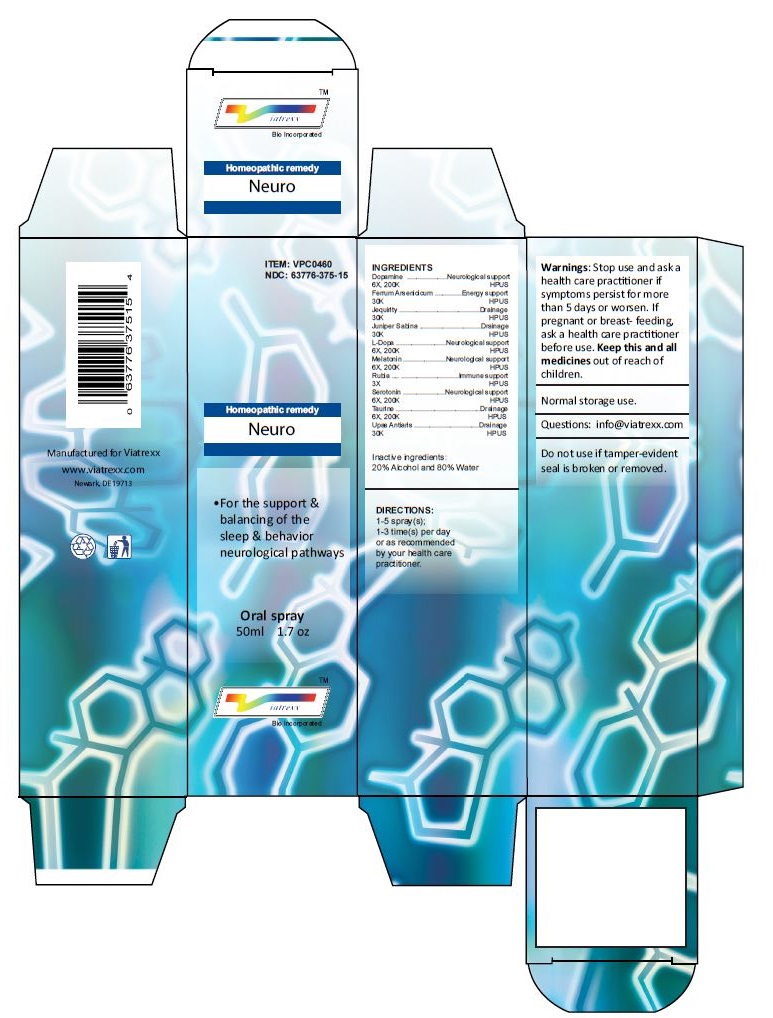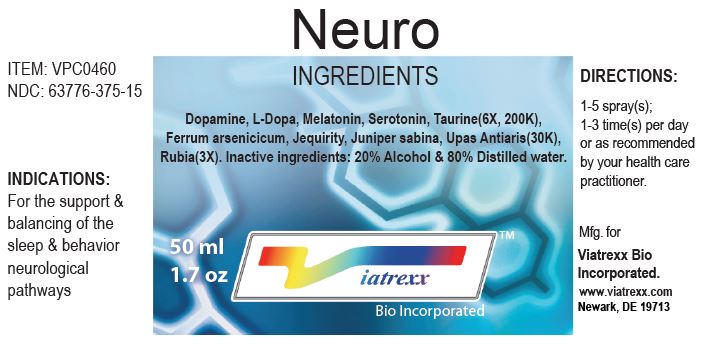 DRUG LABEL: Neuro
NDC: 63776-375 | Form: SPRAY
Manufacturer: VIATREXX BIO INCORPORATED
Category: homeopathic | Type: HUMAN OTC DRUG LABEL
Date: 20221130

ACTIVE INGREDIENTS: DOPAMINE 200 [kp_C]/1 mL; FERROUS ARSENATE 30 [kp_C]/1 mL; ABRUS PRECATORIUS SEED 30 [kp_C]/1 mL; JUNIPERUS SABINA LEAF 30 [kp_C]/1 mL; LEVODOPA 200 [kp_C]/1 mL; MELATONIN 200 [kp_C]/1 mL; RUBIA TINCTORUM WHOLE 3 [hp_X]/1 mL; SEROTONIN 200 [kp_C]/1 mL; TAURINE 200 [kp_C]/1 mL; ANTIARIS TOXICARIA RESIN 30 [kp_C]/1 mL
INACTIVE INGREDIENTS: ALCOHOL; WATER

Neuro

Active Ingredients

Dopamine 6X 200K, Ferrum Arsenicicum 30K, Jequirity 30K, Juniper Sabina 30K, L-Dopa 6X 200K, Melatonin 6X 200K, Rubia 3X, Serotonin 6X 200K, Taurine 6X 200K, Upas Antiaris 30K,

Purpose:

Dopamine | Neurological support
Ferrum Arsenicicum | Energy support
Jequirity | Drainage
Juniper Sabina | Drainage
L-Dopa | Neurological support
Melatonin | Neurological support
Rubia | Immune support
Serotonin | Neurological support
Taurine | Drainage
Upas Antiaris | Drainage

Uses

For the support & balancing of the sleep & behavior neurological pathways

Warnings

Stop use and ask a health care practitioner if symptoms persist for more than 5 days or worsen. If pregnant or breastfeeding, ask a health care practitioner before use.

Dosage

1-5 spray(s); 1-3 time(s) per day or as recommended by your health care practitioner.

KEEP OUT OF REACH OF CHILDREN

Keep this and all medicines out of reach of children.

Other Ingredients

Alcohol and Water

Other Information

Normal storage use.
Do not use if tamper-evident seal is broken or removed.

Questions

info@viatrexx.com

Principal Display Panel

ITEM: VPC0460
NDC 63776-375-15
Homeopathic remedy
Neuro
• For the support & balancing of the sleep & behavior neurological pathways
Oral spray
50ml 1.7 oz
Viatrexx™ Bio Incorporated
Manufactured by Viatrexx
www.viatrexx.com
Newark, DE 19713

Neuro
50 mL
1.7 oz
Viatrexx™ Bio Incorporated
ITEM: VPC0460
NDC: 63776-375-15
INDICATIONS:
For the support & balancing of the sleep & behavior neurological pathways
DIRECTIONS:
1-5 spray(s); 1-3 time(s) per day or as recommended by your health care practitioner.
Mfg. for
Viatrexx Bio Incorporated.
www.viatrexx.com
Newark, DE 19713